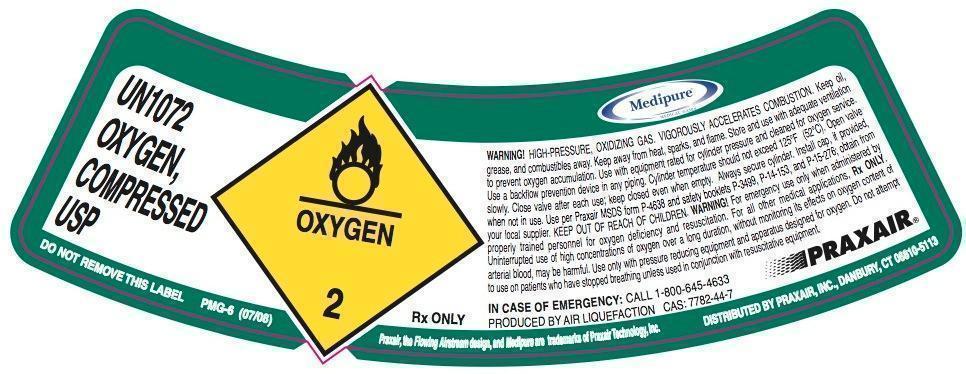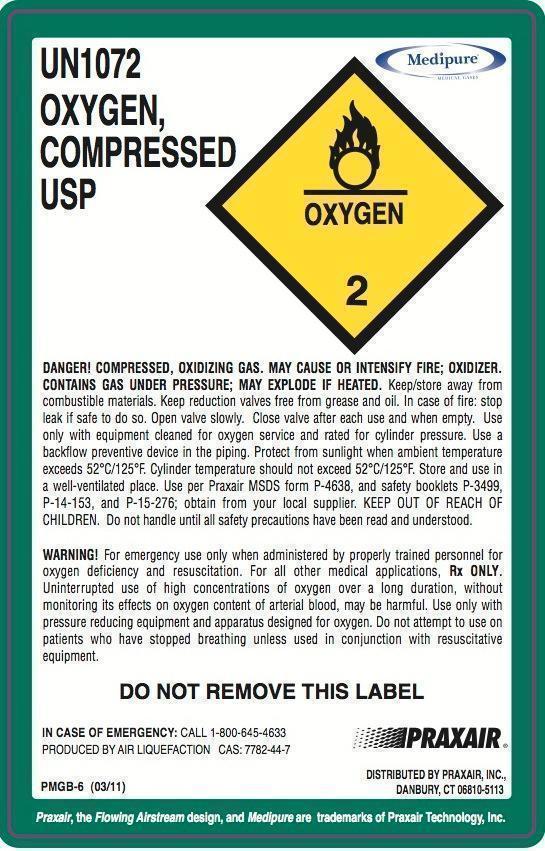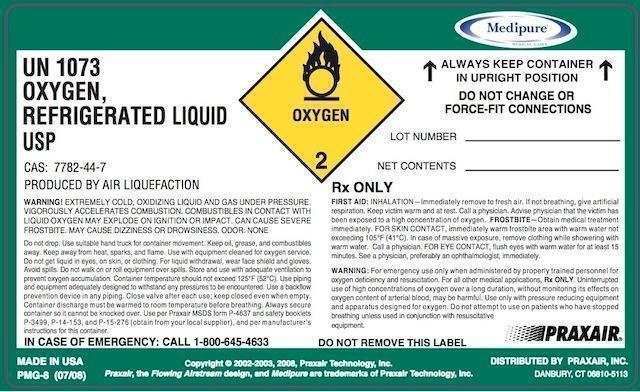 DRUG LABEL: Oxygen
NDC: 59579-011 | Form: GAS
Manufacturer: Praxair Distribution, Inc.
Category: animal | Type: PRESCRIPTION ANIMAL DRUG LABEL
Date: 20211221

ACTIVE INGREDIENTS: Oxygen 990 mL/1 L

Oxygen - Animal

Oxygen Shoulder Label

UN1072 OXYGEN, COMPRESSED USP WARNING! HIGH-PRESSURE, OXIDIZING GAS. VIGOROUSLY ACCELERATES COMBUSTION. Keep oil, grease and combustibles away. Keep away from heat, sparks and flame. Store and use with adequate ventilation to prevent oxygen accumulation. Use with equipment rated for cylinder pressure and cleaned for oxygen service. Use a backflow prevention device in any piping. Cylinder temperature should not exceed 125 deg F (52 deg C). Open valve slowly. Close valve after each use; keep closed even when empty. Always secure cylinder. Install cap, if provided, when not in use. Use per Praxair MSDS form P-4638 and safety booklets P-3499, P-14-153, and P-15-276; obtain from your local supplier. KEEP OUT OF REACH OF CHILDREN. WARNING! For emergency use only when administered by properly trained personnel for oxygen deficiency and resuscitation. For all other medical applications, Rx ONLY. Uninterrupted use of high concentrations of oxygen over a long duration, without monitoring its effects on oxygen content of arterial blood, may be harmful. Use only with pressure reducing equipment and apparatus designed for oxygen. Do not attempt to use on patients who have stopped breathing unless used in conjunction with resuscitative equipment. Rx ONLY CAS 7782-44-7 PRODUCED BY AIR LIQUEFACTION IN CASE OF EMERGENCY: CALL 1-800-645-4633 DISTRIBUTED BY PRAXAIR, INC., DANBURY DO NOT REMOVE THIS LABEL PMG-6 (07/08) Praxair, the flowing airstream design and Medipure are trademarks of Praxair Technology, Inc. DISTRIBUTED BY PRAXAIR, INC, DANBURY, CT 06810-5113 DISTRIBUTED BY PRAXAIR, INC., DANBURY

Oxygen Body Label

UN1072 OXYGEN, COMPRESSED USP DANGER! COMPRESSED, OXIDIZING GAS. MAY CAUSE OR INTENSIFY FIRE; OXIDIZER. CONTAINS GAS UNDER PRESSURE; MAY EXPLODE IF HEATED. Keep/store away from combustible materials. Keep reduction valves free from grease and oil. In case of fire: stop leak if safe to do so. Open valve slowly. Close valve after each use and when empty. Use only with equipment cleaned for oxygen service and rated for cylinder pressure. Use a backflow preventive device in the piping. Protect from sunlight when ambient temperature exceeds 52 deg C/125 deg F. Cylinder temperature should not exceed 52 deg C/125 deg F. Store and use in a well-ventilated place. Use per Praxair MSDS form P-4638, and safety booklets P-3499, P-14-153, and P-15-276; obtain from your local supplier. KEEP OUT OF REACH OF CHILDREN. Do not handle until all safety precautions have been read and understood. WARNING! For emergency use only when administered by properly trained personnel for oxygen deficiency and resuscitation. For all other medical applications, Rx ONLY. Uninterrupted use of high concentrations of oxygen over a long duration, without monitoring its effects on oxygen content of arterial blood, may be harmful. Use only with pressure reducing equipment and apparatus designed for oxygen. Do not attempt to use on patients who have stopped breathing unless used in conjunction with resuscitative equipment DO NOT REMOVE THIS LABEL Rx ONLY CAS 7782-44-7 PRODUCED BY AIR LIQUEFACTION IN CASE OF EMERGENCY: CALL 1-800-645-4633 DISTRIBUTED BY PRAXAIR, INC., DANBURY PMGB-6 (03/11) Praxair, the flowing airstream design and Medipure are trademarks of Praxair Technology, Inc. DISTRIBUTED BY PRAXAIR, INC, DANBURY, CT 06810-5113

Oxygen Refrigerated

UN1073 OXYGEN, REFRIGERATED LIQUID USP ALWAYS KEEP CONTAINER IN UPRIGHT POSITION. DO NOT CHANGE OR FORCE-FIT CONNECTIONS LOT # NET CONTENTS WARNING! EXTREMELY COLD, OXIDIZING LIQUID AND GAS UNDER PRESSURE. VIGOROUSLY ACCELERATES COMBUSTION. COMBUSTIBLES IN CONTACT WITH LIQUID OXYGEN MAY EXPLODE ON IGNITION OR IMPACT. CAN CAUSE SEVERE FROSTBITE. MAY CAUSE DIZZINESS OR DROWSINESS. ODOR: NONE Do not drop. Use suitable hand truck for container movement. Keep oil, grease, and combustibles away. Keep away from heat, sparks, and flame. Use with equipment cleaned for oxygen service. Do not get liquid in eyes, on skin, or clothing. For liquid withdrawal, wear face shield and gloves. Avoid spills. Do not walk on or roll equipment over spills. Store and use with adequate ventilation to prevent oxygen accumulation. Container temperature should not exceed 125 deg F (52 deg C). Use piping and equipment adequately designed to withstand any pressures to be encountered. Use a backflow prevention device in any piping. Close valve after each use; keep closed even when empty. Container discharge must be warmed to room temperature before breathing. Always secure container so it cannot be knocked over. Use per Praxair MSDS form P-4637 and safety booklets P-3499, P-14-153, and P-15-276 (obtain from your local supplier), and per manufacturer’s instructions for this container. RX ONLY FIRST AID: INHALATION—immediately remove to fresh air. If not breathing, give artificial respiration. Keep victim warm and at rest. Call a physician. Advise physician that the victim has been exposed to a high concentration of oxygen. FROSTBITE—Obtain medical treatment immediately. FOR SKIN CONTACT, immediately warm frostbite area with warm water not exceeding 105 deg F (41 deg C). In case of massive exposure, remove clothing while showering with warm water. Call a physician. FOR EYE CONTACT, flush eyes with warm water for at least 15 minutes. See a physician, preferably an ophthalmologist, immediately. WARNING: For emergency use only when administered by properly trained personnel for oxygen deficiency and resuscitation. For all other medical applications, Rx ONLY. Uninterrupted use of high concentrations of oxygen over a long duration, without monitoring its effects on oxygen content of arterial blood, may be harmful. Use only with pressure reducing equipment and apparatus designed for oxygen. Do not attempt to use on patients who have stopped breathing unless used in conjunction with resuscitative equipment. DO NOT REMOVE THIS LABEL Rx ONLY CAS 7782-44-7 PRODUCED BY AIR LIQUEFACTION IN CASE OF EMERGENCY: CALL 1-800-645-4633 PMG-8 (07/08) Copyright @ 2002-2003, 2008. Praxair Technology, Inc.Praxair, the flowing airstream design and Medipure are trademarks of Praxair Technology, Inc. DISTRIBUTED BY PRAXAIR, INC, DANBURY, CT 06810-5113